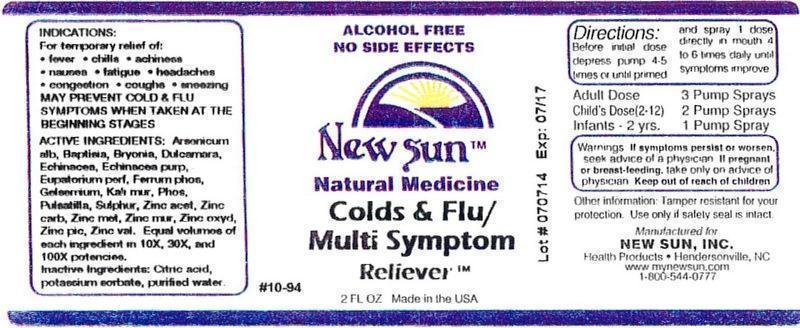 DRUG LABEL: Colds and Flu/Multi Symptom Reliever
NDC: 66579-0090 | Form: LIQUID
Manufacturer: New Sun Inc.
Category: homeopathic | Type: HUMAN OTC DRUG LABEL
Date: 20140820

ACTIVE INGREDIENTS: ARSENIC TRIOXIDE 10 [hp_X]/59 mL; BAPTISIA TINCTORIA ROOT 10 [hp_X]/59 mL; BRYONIA ALBA ROOT 10 [hp_X]/59 mL; SOLANUM DULCAMARA TOP 10 [hp_X]/59 mL; ECHINACEA, UNSPECIFIED 10 [hp_X]/59 mL; ECHINACEA PURPUREA 10 [hp_X]/59 mL; FERROSOFERRIC PHOSPHATE 10 [hp_X]/59 mL; GELSEMIUM SEMPERVIRENS ROOT 10 [hp_X]/59 mL; POTASSIUM CHLORIDE 10 [hp_X]/59 mL; PHOSPHORUS 10 [hp_X]/59 mL; PULSATILLA VULGARIS 10 [hp_X]/59 mL; SULFUR 10 [hp_X]/59 mL; ZINC ACETATE ANHYDROUS 10 [hp_X]/59 mL; ZINC CARBONATE 10 [hp_X]/59 mL; ZINC 10 [hp_X]/59 mL; ZINC CHLORIDE 10 [hp_X]/59 mL; ZINC OXIDE 10 [hp_X]/59 mL; ZINC PICRATE NONAHYDRATE 10 [hp_X]/59 mL; ZINC VALERATE DIHYDRATE 10 [hp_X]/59 mL
INACTIVE INGREDIENTS: CITRIC ACID MONOHYDRATE; POTASSIUM SORBATE; WATER

Colds and Flu/Multi Symptom Reliever

DOSAGE AND ADMINISTRATION

Directions: Before initial dose depress pump 4-5 times or until primed and spray 1 dose directly in mouth 4 to 6 times daily until symptoms improve.

Adult Dose: 3 Pump Sprays

Child's Dose (2-12): 2 Pump Sprays

Infants - 2 yrs: 1 Pump Spray

WARNINGS

Warnings: If symptoms persist or worsen, seek advice of physician. If pregnant or breast-feeding, take only on advice of physician.

Keep out of reach of children.

Other information: Tamper resistant for your protection. Use only if safety seal is intact.

PURPOSE

Indications: For temporary relief of: •fever •chills •achiness •nausea •fatigue •headaches •congestion •coughs •sneezing

ACTIVE INGREDIENT

Active Ingredients: Arsenicum album, Baptisia tinctoria, Bryonia, Dulcamara, Echinacea, Echinacea purpurea, Eupatorium purpureum, Ferrum phosphoricum, Gelsemium sempervirens, Kali muriaticum, Phosphorus, Pulsatilla, Sulphur, Zincum aceticum, Zincum carbonicum, Zincum metallicum, Zincum muriaticum, Zincum oxydatum, Zincum picricum, Zincum valerianicum. Equal volumes of each ingredient in 10X, 30X, and 100X potencies.

Inactive Ingredient: Citric acid, potassium sorbate, purified water.

Indications: For temporary relief of:

- fever
- chills
- achiness
- nausea
- fatigue
- headaches
- congestion
- coughs
- sneezing